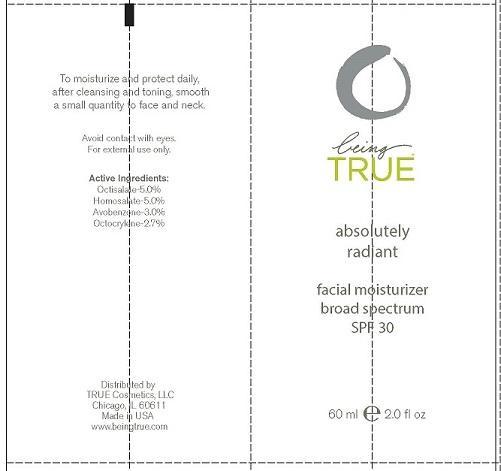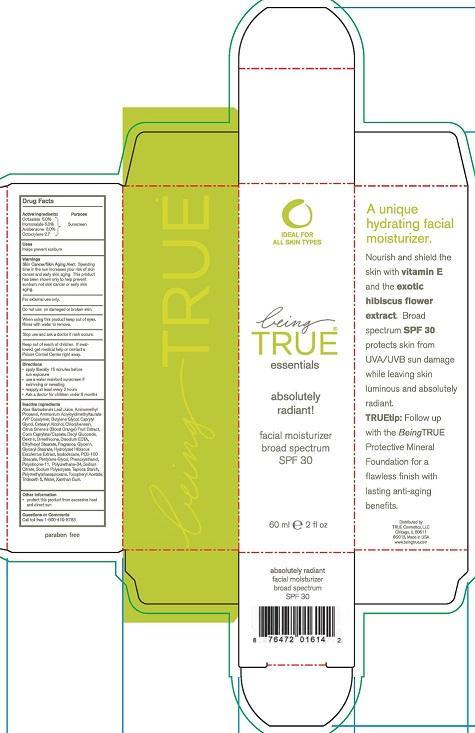 DRUG LABEL: BEING TRUE ESSENTIALS ABSOLUTELY RADIANT
NDC: 60724-101 | Form: LOTION
Manufacturer: TRUE Cosmetics LLC
Category: otc | Type: HUMAN OTC DRUG LABEL
Date: 20130919

ACTIVE INGREDIENTS: OCTISALATE 5 g/100 mL; HOMOSALATE 5 g/100 mL; AVOBENZONE 3 g/100 mL; OCTOCRYLENE 2.7 g/100 mL
INACTIVE INGREDIENTS: ALOE VERA LEAF; AMINOMETHYLPROPANOL; AMMONIUM ACRYLOYLDIMETHYLTAURATE/VP COPOLYMER; BUTYLENE GLYCOL; CAPRYLYL GLYCOL; CETOSTEARYL ALCOHOL; CHLORPHENESIN; CITRUS SINENSIS WHOLE; COCO-CAPRYLATE/CAPRATE; DECYL GLUCOSIDE; ICODEXTRIN; PEG-100 STEARATE; PENTYLENE GLYCOL; PHENOXYETHANOL; POLYSILICONE-15; POLYBUTENE (1400 MW); SODIUM CITRATE; SODIUM POLYACRYLATE (8000 MW); STARCH, TAPIOCA; POLYMETHYLSILSESQUIOXANE (11 MICRONS); ALPHA-TOCOPHEROL ACETATE; TRIDECETH-6; WATER; XANTHAN GUM

ACTIVE INGREDIENTS:

OCTISALATE 5.0%

HOMOSALATE 5.0%

AVOBENZONE 3.0%

OCTOCRYLENE 2.7%

PURPOSE:

SUNSCREEN

USES

HELPS PREVENT SUNBURN

WARNINGS

SKN CANCER/SKIN AGING ALERT: SPENDING TIME IN THE SUN INCREASES YOU RISK OF SKIN CANCER AND EARLY SKIN AGING. THIS PRODUCT HAS BEEN SHOWN ONLY TO PREVENT SUNBURN, NOT SKIN CANCER OR EARLY AGING.

FOR EXTERNAL USE ONY.

DO NOT USE ON DAMAGED OR BROKEN SKIN.

WHEN USING THIS PRODUCT KEEP OUT OF EYES.

RINSE WITH WATER TO REMOVE.

STOP USE AND ASK A DOCTOR IF RASH OCCURS.

KEEP OUT OF REACH OF CHILDREN. IF SWALLOWED, GET MEDICAL HELP OR CONTACT A POISON CONTROL CENTER RIGHT AWAY.

DIRECTIONS

- APPLY LIBERALLY 15 MINUTES BEFORE SUN EXPOSURE
- USE A WATER RESISTANT SUNSCREEN IF SWIMMING OR SWEATING
- REAPPLY AT LEAST EVERY 2 HOURS
- ASK A DOCTOR FOR CHILDREN UNDER 6 MONTHS

INACTIVE INGREDENTS

ALOE BARBADENSIS LEAF JUICE, ALOE BARBADENSIS LEAF EXTRACT, AMINOMETHYL PROPANOL, AMMONIUM ACRYLOYLDIMETHYLTAURATE/VP COPOLYMER, BUTYLENE GLYCOL, CAPRYLYL GLYCOL, CETEARYL ALCOHOL, CHLORPHENESIN, CITRUS SINENSIS (BLOOD ORANGE) FRUIT EXTRACT, COCO CAPRYLATE/CAPRATE, DECYL GLUCOSIDE, DEXTRIN, DIMETHICONE, DISODIUM EDTA, ETHYHEXYL STEARATE, HYDROLYZED HIBISCUS ESCULENTUS EXTRACT, ISODODECANE, PEG-100 STEARATE, PENTYLENE GLYCOL, PHENOXYETHANOL, POLYSILICONE-11, POLYURETHANE-34, SODIUM CITRATE, SODIUM POLYACRYLATE, TAPIOCA STARCH, POLYMETHYLSILSESQUIOXANE, TOCOPHERYL ACETATE, TRIDECETH 6, WATER, XANTHAN GUM.

OTHER INFORMATION

- PROTECT THIS PRODUCT FROM EXCESSIVE HEAT AND DIRECT SUN.

QUESTIONS OR COMMENTS

CALL TOLL FREE 1-800-419-8783